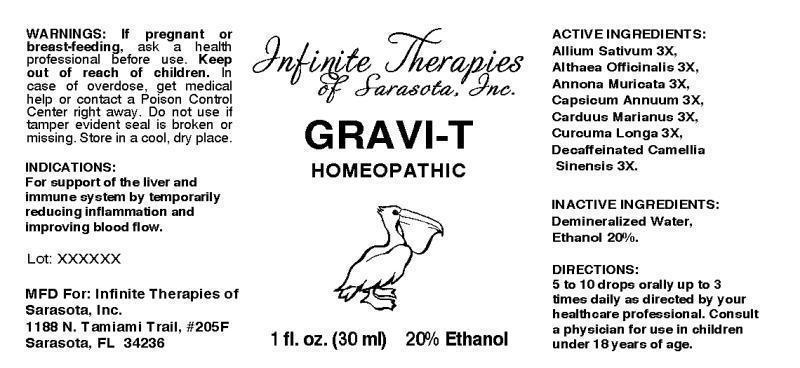 DRUG LABEL: GRAVI-T
NDC: 54005-0001 | Form: LIQUID
Manufacturer: Infinite Therapies of Sarasota, Inc.
Category: homeopathic | Type: HUMAN OTC DRUG LABEL
Date: 20130806

ACTIVE INGREDIENTS: GARLIC 3 [hp_X]/1 mL; ALTHAEA OFFICINALIS ROOT 3 [hp_X]/1 mL; SOURSOP 3 [hp_X]/1 mL; CAPSICUM 3 [hp_X]/1 mL; SILYBUM MARIANUM SEED 3 [hp_X]/1 mL; TURMERIC 3 [hp_X]/1 mL; GREEN TEA LEAF 3 [hp_X]/1 mL
INACTIVE INGREDIENTS: WATER; ALCOHOL

DRUG FACTS:

ACTIVE INGREDIENTS:

Allium Sativum 3X, Althaea Officinalis 3X, Annona Muricata 3X, Capsicum Annum 3X, Carduus Marianus 3X, Curcuma Longa 3X, Decaffeinated Camellia Sinensis 3X.

INDICATIONS:

For support of the liver and immune system by temporarily reducing inflammation and improving blood flow.

WARNINGS:

If pregnant or breast-feeding, ask a health professional before use.

Keep out of reach of children. In case of overdose, get medical help or contact a Poison Control Center right away.

Do not use if tamper evident seal is broken or missing.

STORAGE:

Store in cool, dry place.

DIRECTIONS:

5 to 10 drops orally up to 3 times daily as directed by your healthcare professional. Consult a physician for use in children unter 18 years of age.

INACTIVE INGREDIENTS:

Demineralized Water, Ethanol 20%

Keep out of reach of children. In case of overdose, get medical help or contact a Poison Control Center right away.

INDICATIONS:

For support of the liver and immune system by temporarily reducing inflammation and improving blood flow.

QUESTIONS:

MFD For: Infinite Therapies of Sarasota, Inc.

1188 N. Tamiami Trail, #205F

Sarasota, FL 34236

PACKAGE DISPLAY LABEL:

Infinite Therapies of Sarasota, Inc.

GRAVI-T

HOMEOPATHIC

1 fl. oz. (30 mL) 20% Ethanol